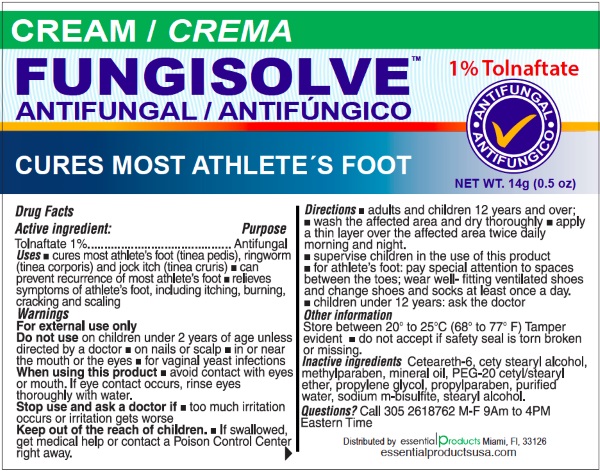 DRUG LABEL: FUNGISOLVE TOLNAFTATE ANTIFUNGAL
NDC: 70242-107 | Form: CREAM
Manufacturer: Dannso Corp./d.b.a. Essential Products
Category: otc | Type: HUMAN OTC DRUG LABEL
Date: 20160430

ACTIVE INGREDIENTS: TOLNAFTATE 1 g/100 g
INACTIVE INGREDIENTS: WATER; MINERAL OIL; GLYCERIN; PEG-15 GLYCERYL STEARATE; GLYCERYL MONOSTEARATE; STEARIC ACID; CARBOMER HOMOPOLYMER TYPE C (ALLYL PENTAERYTHRITOL CROSSLINKED); MYRISTOYL/PALMITOYL OXOSTEARAMIDE/ARACHAMIDE MEA; PHOSPHATE ION; CHLOROCRESOL

FUNGISOLVE Tolnaftate Antifungal Cream

Active Ingredients

Tolnaftate 1%

Purpose

Antifungal

Uses

cures most athlete's foot (tinea pedis), ringworm (tinea corporis) and jock itch (tinea cruris)

can prevent recurrence of most athlete's foot

relieves sympotoms of athelete's foot including itching, burning, cracking and scaling.

Warnings

For external use only

Do not use

- children under 2 years of age unless directed by a doctor
- on nails or scalp
- in or near the mouth or the eyes
- for vaginal yeast infections

Stop use and ask a doctor if

too much irritation occurs or irratation gets worse

When using this product

avoid contact with the eyes or mouth. If eye contacts occurs, rinse eyes thoroughtly with water.

Keep out of reach of children.

If swallowed, get medical help or contact a Poison Control Center immediately.

Directions

- adults and children 12 years and over
- wash the affected area and dry thoroughly
- apply a thin layer over affected area twice daily morning and night
- supervis children in the use of this product
- for athlete's foot, pay special attention to spaces between the toes: wear well-fitting ventilated shoes and change shoes and socks at least once a day.

Other Information

store between 20 to 25 C (68 to 77)F

do not accept if safety seal is torn broken or missing.

Inactive Ingredients

Ceteareth-6, cety stearyl alcohol, methylparaben, mineral oil, PEG-20 cetyl/stearyl ether, propylene glycol, propylparaben, purified water, sodium m-bisulfite, stearyl alcohol.

Questions?

Call 305 2618762 M-F 9AM to 4PM Eastern Time

Distributed by:

Essential Productd Miami, FL, 33126 www.essentialproductsusa.com